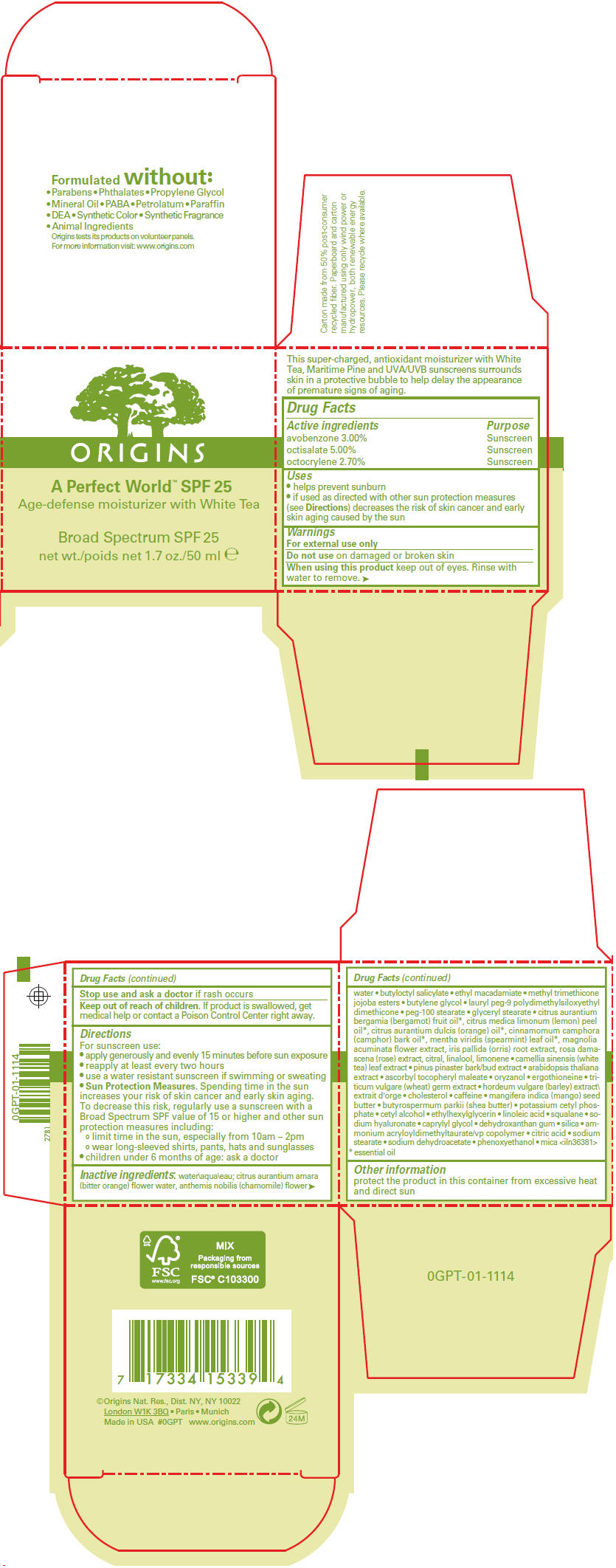 DRUG LABEL: A PERFECT WORLD
NDC: 59427-702 | Form: LOTION
Manufacturer: ORIGINS NATURAL RESOURCES INC
Category: otc | Type: HUMAN OTC DRUG LABEL
Date: 20120301

ACTIVE INGREDIENTS: OCTISALATE 5 mL/100 mL; AVOBENZONE 3 mL/100 mL; OCTOCRYLENE 2.7 mL/100 mL
INACTIVE INGREDIENTS: WATER; CITRUS AURANTIUM FRUIT; CHAMOMILE; BUTYLOCTYL SALICYLATE; ETHYL MACADAMIATE; METHYL TRIMETHICONE; BUTYLENE GLYCOL; PEG-100 STEARATE; GLYCERYL MONOSTEARATE; BERGAMOT OIL; LEMON OIL; ORANGE OIL; CAMPHOR OIL; SPEARMINT OIL; MAGNOLIA ACUMINATA FLOWER; IRIS PALLIDA ROOT; ROSA DAMASCENA FLOWER; CITRAL; LINALOOL, (+/-)-; MARITIME PINE; GAMMA ORYZANOL; ERGOTHIONEINE; WHEAT GERM; BARLEY; CHOLESTEROL; CAFFEINE; MANGIFERA INDICA SEED BUTTER; SHEA BUTTER; POTASSIUM CETYL PHOSPHATE; CETYL ALCOHOL; ETHYLHEXYLGLYCERIN; LINOLEIC ACID; SQUALANE; HYALURONATE SODIUM; CAPRYLYL GLYCOL; SILICON DIOXIDE; AMMONIUM ACRYLOYLDIMETHYLTAURATE/VP COPOLYMER; CITRIC ACID MONOHYDRATE; SODIUM STEARATE; SODIUM DEHYDROACETATE; PHENOXYETHANOL; MICA

A Perfect World™ SPF 25
Age-defense moisturizer with White Tea

Drug Facts

ACTIVE INGREDIENT

Active ingredients | Purpose
avobenzone 3.00% | Sunscreen
octisalate 5.00% | Sunscreen
octocrylene 2.70% | Sunscreen

Uses

- helps prevent sunburn
- if used as directed with other sun protection measures (see Directions) decreases the risk of skin cancer and early skin aging caused by the sun

Warnings

For external use only

Do not use on damaged or broken skin

When using this product keep out of eyes. Rinse with water to remove.

STOP USE

Stop use and ask a doctor if rash occurs

Keep out of reach of children. If product is swallowed, get medical help or contact a Poison Control Center right away.

Directions

For sunscreen use:

- apply generously and evenly 15 minutes before sun exposure
- reapply at least every two hours
- use a water resistant sunscreen if swimming or sweating
- Sun Protection Measures. Spending time in the sun increases your risk of skin cancer and early skin aging. To decrease this risk, regularly use a sunscreen with a Broad Spectrum SPF value of 15 or higher and other sun protection measures including:
  - limit time in the sun, especially from 10am – 2pm
  - wear long-sleeved shirts, pants, hats and sunglasses
- children under 6 months of age: ask a doctor

Inactive ingredients

water; citrus aurantium amara (bitter orange) flower water, anthemis nobilis (chamomile) flower water ∙ butyloctyl salicylate ∙ ethyl macadamiate ∙ methyl trimethicone jojoba esters ∙ butylene glycol ∙ lauryl peg-9 polydimethylsiloxyethyl dimethicone ∙ peg-100 stearate ∙ glyceryl stearate ∙ citrus aurantium bergamia (bergamot) fruit oil [essential oil] , citrus medica limonum (lemon) peel oil, citrus aurantium dulcis (orange) oil, cinnamomum camphora (camphor) bark oil, mentha viridis (spearmint) leaf oil, magnolia acuminata flower extract, iris pallida (orris) root extract, rosa damascena (rose) extract, citral, linalool, limonene ∙ camellia sinensis (white tea) leaf extract ∙ pinus pinaster bark/bud extract ∙ arabidopsis thaliana extract ∙ ascorbyl tocopheryl maleate ∙ oryzanol ∙ ergothioneine ∙ triticum vulgare (wheat) germ extract ∙ hordeum vulgare (barley) extract ∙ cholesterol ∙ caffeine ∙ mangifera indica (mango) seed butter ∙ butyrospermum parkii (shea butter) ∙ potassium cetyl phosphate ∙ cetyl alcohol ∙ ethylhexylglycerin ∙ linoleic acid ∙ squalane ∙ sodium hyaluronate ∙ caprylyl glycol ∙ dehydroxanthan gum ∙ silica ∙ ammonium acryloyldimethyltaurate/vp copolymer ∙ citric acid ∙ sodium stearate ∙ sodium dehydroacetate ∙ phenoxyethanol ∙ mica <iln36381>

Other information

protect the product in this container from excessive heat and direct sun

©Origins Nat. Res., Dist. NY, NY 10022

PRINCIPAL DISPLAY PANEL - 50 ml Jar Carton

ORIGINS

A Perfect World™ SPF 25
Age-defense moisturizer with White Tea

Broad Spectrum SPF 25

net wt. 1.7 oz./50 ml e